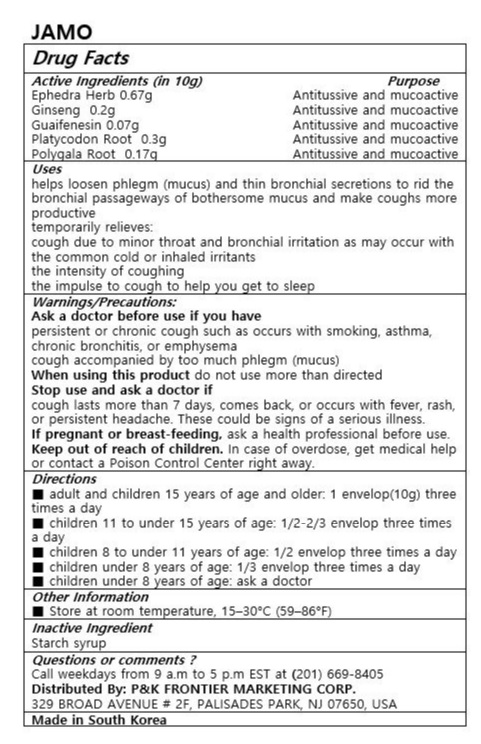 DRUG LABEL: JAMO
NDC: 72689-0031 | Form: GEL
Manufacturer: OASIS TRADING
Category: otc | Type: HUMAN OTC DRUG LABEL
Date: 20181213

ACTIVE INGREDIENTS: GUAIFENESIN 0.07 g/10 g; EPHEDRA SINICA STEM 0.67 g/10 g; ASIAN GINSENG 0.2 g/10 g; POLYGALA TENUIFOLIA ROOT 0.17 g/10 g; PLATYCODON GRANDIFLORUS ROOT 0.3 g/10 g
INACTIVE INGREDIENTS: CORN SYRUP

ACTIVE INGREDIENT

Ephedra Herb 0.67g

Ginseng 0.2g

Guaifenesin 0.07g

Platycodon Root 0.3g

Polygala Root 0.17g

PURPOSE

helps loosen phlegm (mucus) and thin bronchial secretions to rid the bronchial passageways of bothersome mucus and make coughs more productive

temporarily relieves:

cough due to minor throat and bronchial irritation as may occur with the common cold or inhaled irritants

the intensity of coughing

the impulse to cough to help you get to sleep

Keep out of reach of children

INDICATIONS AND USAGE

■ adult and children 15 years of age and older: 1 envelop(10g) three times a day

■ children 11 to under 15 years of age: 1/2-2/3 envelop three times a day

■ children 8 to under 11 years of age: 1/2 envelop three times a day

■ children under 8 years of age: 1/3 envelop three times a day

■ children under 8 years of age: ask a doctor

Ask a doctor before use if you have

persistent or chronic cough such as occurs with smoking, asthma, chronic bronchitis, or emphysema

cough accompanied by too much phlegm (mucus)

When using this product do not use more than directed

Stop use and ask a doctor if

cough lasts more than 7 days, comes back, or occurs with fever, rash, or persistent headache. These could be signs of a serious illness.

If pregnant or breast-feeding, ask a health professional before use.

Keep out of reach of children. In case of overdose, get medical help or contact a Poison Control Center right away.

INACTIVE INGREDIENT

starch syrup

DOSAGE AND ADMINISTRATION

For oral use only